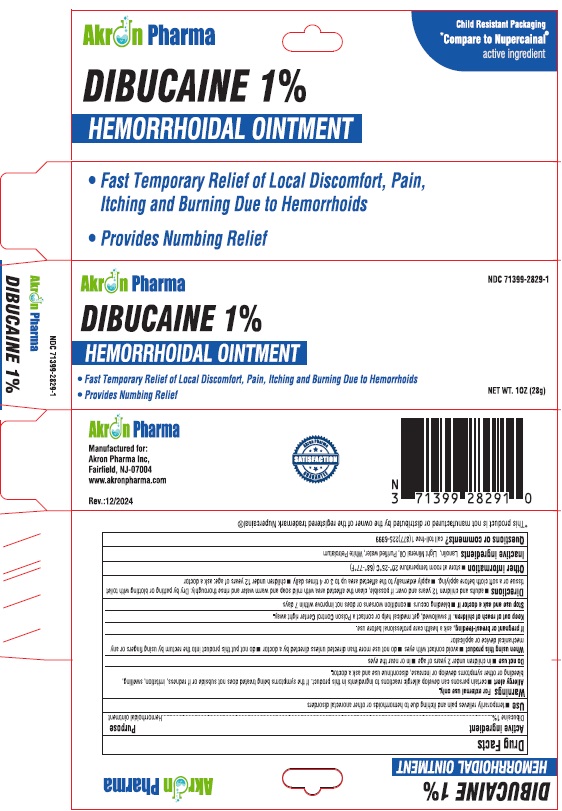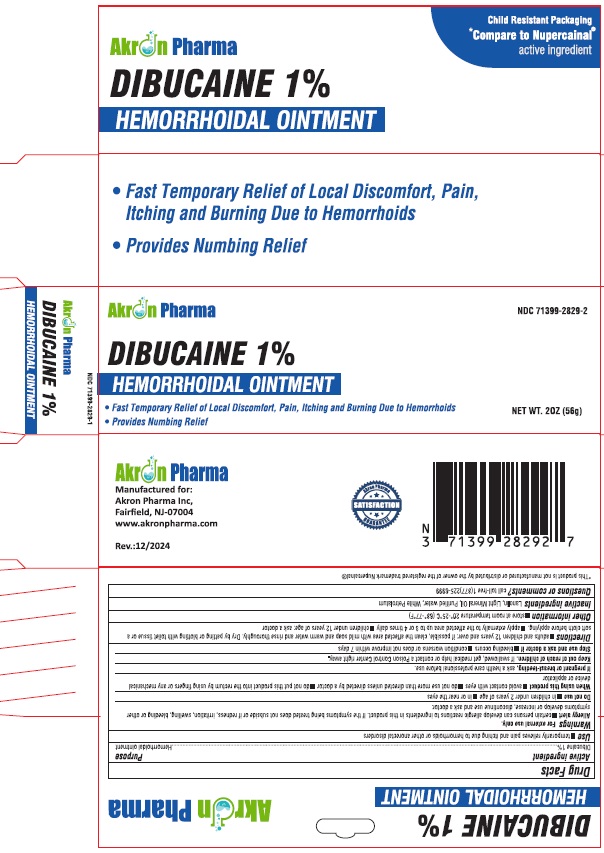 DRUG LABEL: Dibucaine
NDC: 71399-2829 | Form: OINTMENT
Manufacturer: Akron Pharma Inc.
Category: otc | Type: HUMAN OTC DRUG LABEL
Date: 20250112

ACTIVE INGREDIENTS: DIBUCAINE 0.28 g/28 g
INACTIVE INGREDIENTS: LANOLIN; LIGHT MINERAL OIL; WATER; WHITE PETROLATUM

Dibucaine Ointment

Drug Facts

Active ingredient Purpose

Dibucaine 1% Hemorrhoidal ointment

Uses

temporanly relieves pain and nching due to hemorrhoids or other anorectal disorders

Warninigs

For External Use Only

Allergy alert

- certain persons can develop allergic reactions to ingredients in this product. If the symptoms being treated does not subside or redness, irritation, swelling, bleeding or other symptoms develop or increase, discontinue use and ask a doctor.

Do not use

- in children under 2 years at age
- in or near the eyes

When using this product

- avoid contact wnh eyes
- do not use more than directed unless directed by a doctor
- do not put this product into the rectum by using fingers or any mechanical device or applicator

lf pregnant or breast feeding, ask a health care professional before use.

Keep out of reach of children. If swallowed, get medical help or contact a Poison Control Center right away.

Stop use and ask a doctor if

- bleeding occurs
- condition worsens or does not improve wnhin 7 days

Directions

- adults and children 12 years and over: if possible, clean the affected area with mild soap and wann water and nnse thoroughly. Dry by patting or blotting withh toilet tissue or a soft cloth before applying.
- apply externally to the affected area up to 3 or 4 times daily
- children under 12 years of age: ask a doctor

Inactive Ingredients

Lanolin, Light Mineral Oil, Purified water, White Petrotalum

STORAGE AND HANDLING

Store at room temperature 20o-25oC (68o-77oF)

Questions or Comments?

call toll-free 1(877)225-6999

Manufactured for
Akron Pharma, Inc.,
Fairfeld, NJ - 07004